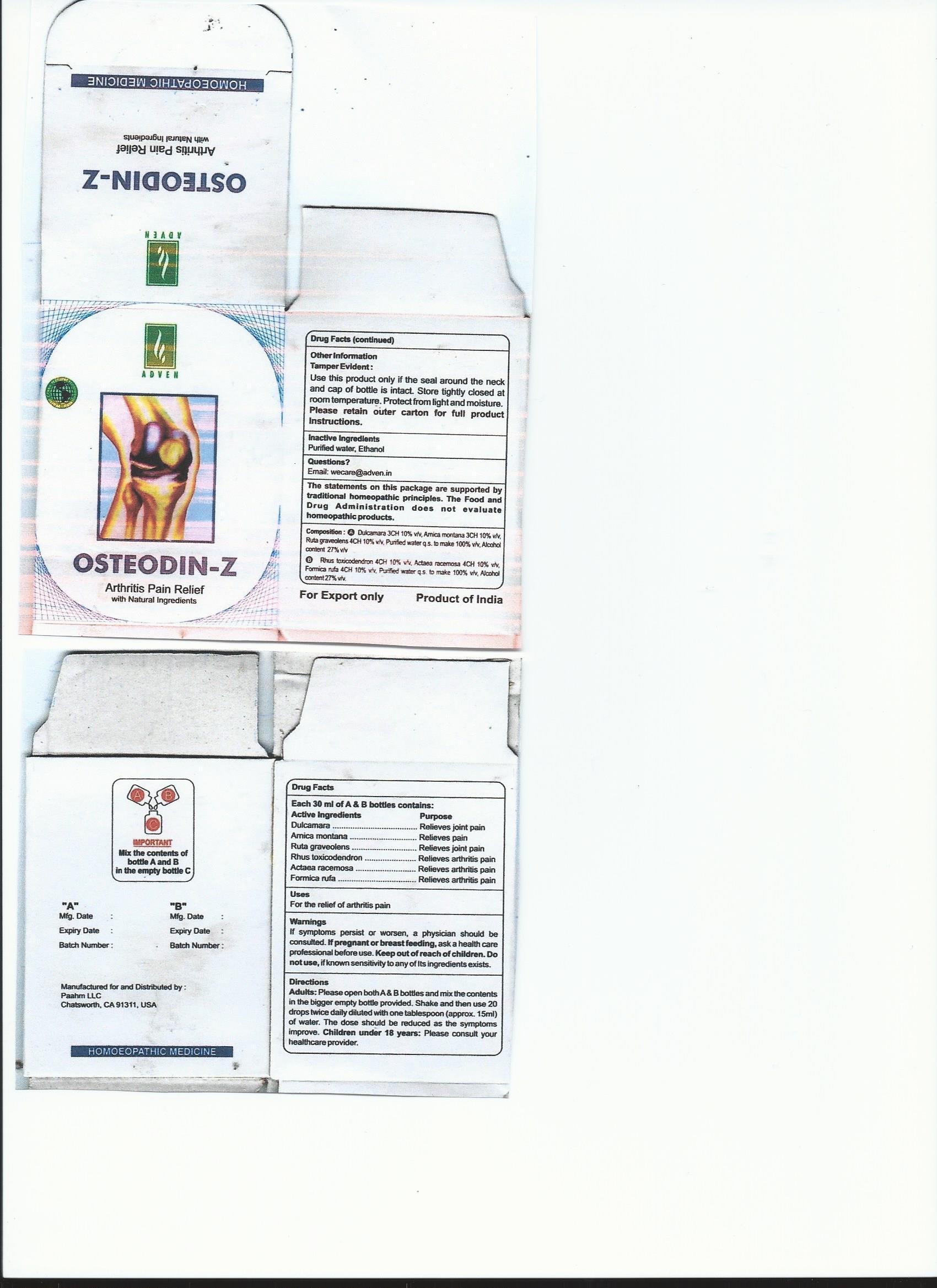 DRUG LABEL: Osteodin-Z
NDC: 69825-001 | Form: LIQUID
Manufacturer: Adven Biotech Private Limited
Category: homeopathic | Type: HUMAN OTC DRUG LABEL
Date: 20150523

ACTIVE INGREDIENTS: SOLANUM DULCAMARA TOP 3 [hp_C]/30 mL; RUTA GRAVEOLENS FLOWERING TOP 4 [hp_C]/30 mL; TOXICODENDRON PUBESCENS LEAF 4 [hp_C]/30 mL; FORMICA RUFA 4 [hp_C]/30 mL; ACTAEA RACEMOSA WHOLE 4 [hp_C]/30 mL; ARNICA MONTANA 3 [hp_C]/30 mL
INACTIVE INGREDIENTS: WATER; ALCOHOL

Drug Facts

Active Ingredients

Dulcamara

Amica montana

Ruta graveolens

Rhus toxicodendron

Actaea racemosa

Formica rufa

Purpose

Dulcamara..........Relieves joint pain

Amica montana...Relieves pain

Ruta graveolens..Relieves joint pain

Rhus toxicodendron...Relieves arthritis pain

Actaea racemosa....Relieves arthritis pain

Formica rufa.......Relieves arthritis pain

Uses

for the relief of arthritis pain

Warnings

If symptoms persist or worsen, a physician should be

consulted. If pregnant or breast feeding, ask a health care

professional before use. Keep out of reach of children. Do not

use, if known sensitivity to any of its ingredients exists.

Keep out of reach of children.

Directions

Adults: Please open both A and B bottles and mix the contents

in the bigger empty bottle provided. Shake and then use 20

drops twice daily diluted with one tablespoon (approx. 15 ml)

of water. The dose should be reduced as the symptoms

improve. Children under 18 years : Please consult your

healthcare provider.

Other Information

Tamper Evident:

Use this product only if the seal around the neck and

cap of the bottle is intact. Store tightly closed at

room temperature. Protect from light and moisture.

Please retain outer carton for full product instructions.

Inactive Ingredients

Purified water, Ethanol

Questions?

Email: wecare@adven.in

DESCRIPTION

The statements on this package are supported by

traditional homeopathic principles. The Food and Drug

Administration does not evaluate homeopathic products.